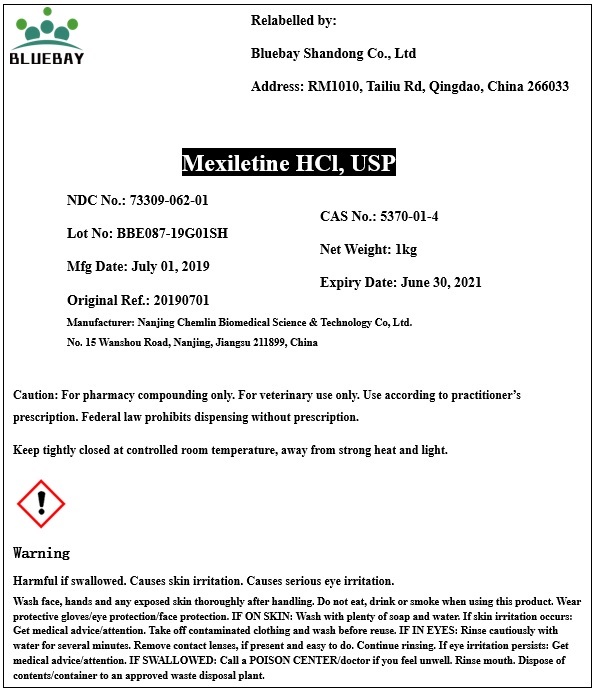 DRUG LABEL: Mexiletine Hydrochloride
NDC: 73309-062 | Form: POWDER
Manufacturer: BLUEBAY SHANDONG CO.,LTD
Category: other | Type: BULK INGREDIENT
Date: 20191129

ACTIVE INGREDIENTS: MEXILETINE HYDROCHLORIDE 1 kg/1 kg

Mexiletine Hydrochloride